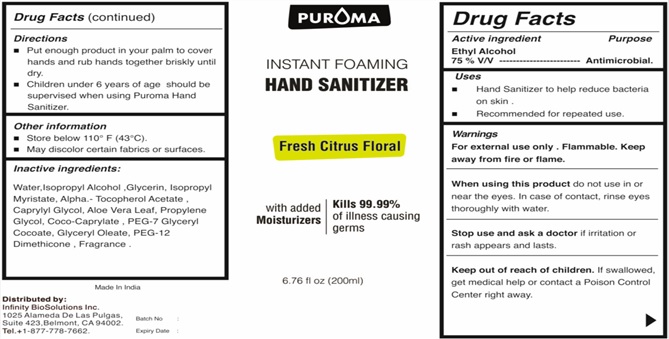 DRUG LABEL: PUROMA Instant Foaming Hand Sanitizer  with   Fragrance citrus floral
NDC: 80948-018 | Form: LIQUID
Manufacturer: ZENITH MICRO CONTROL
Category: otc | Type: HUMAN OTC DRUG LABEL
Date: 20231214

ACTIVE INGREDIENTS: ALCOHOL 75 mL/100 mL
INACTIVE INGREDIENTS: WATER; ISOPROPYL ALCOHOL; GLYCERIN; ISOPROPYL MYRISTATE; .ALPHA.-TOCOPHEROL ACETATE; CAPRYLYL GLYCOL; PROPYLENE GLYCOL; COCO-CAPRYLATE; ALOE VERA LEAF; GLYCERYL OLEATE; PEG-7 GLYCERYL COCOATE; PEG-12 DIMETHICONE; FRAGRANCE FRESH CITRUS FLORAL ORC1501495

Active ingredient

Alcohol 75 % V/V

Purpose

Antimicrobial.

Uses

Hand Sanitizer to help reduce bacteria on skin.
Recommended for repeated use.

Warnings

• For external use only. Flammable. Keep away from fire or flame.
• When using this product do not use in or near the eyes. In case of contact, rinse eyes thoroughly with water.
• Stop use and ask a doctor if irritation or rash appears and lasts.

Keep out of reach of children

If swallowed, get medical help or contact a Poison Control Center right away.

Directions

• Put enough product in your palm to cover hands and rub hands together briskly until dry.
• Children under 6 years of age should be supervised when using Puroma Hand Sanitizer.

Inactive ingredients

Water, Isopropyl Alcohol ,Glycerin, Isopropyl Myristate, Alpha.- Tocopherol Acetate , Caprylyl Glycol, Aloe Vera Leaf, Propylene Glycol, Coco-Caprylate , PEG-7 Glyceryl Cocoate, Glyceryl Oleate, PEG-12 Dimethicone, Fragrance Fresh Citrus Floral ORC1501495

Other information

• Store below 110°F (430°C)
• May discolor certain fabrics or surfaces